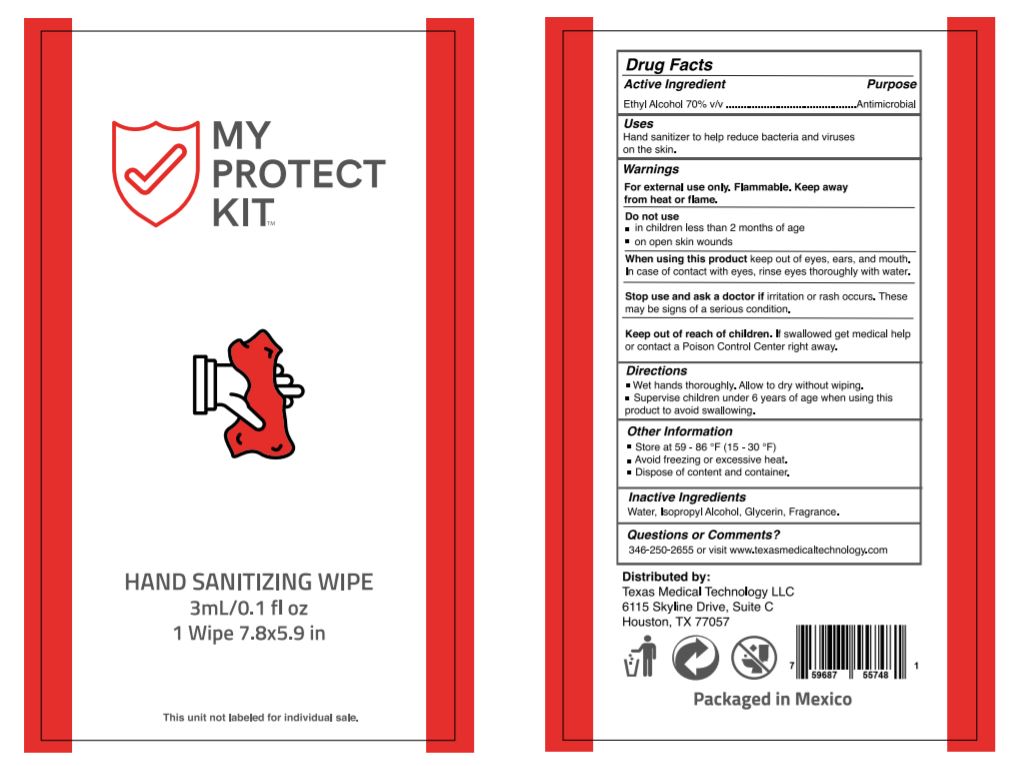 DRUG LABEL: MPK ALCOHOL SANITIZING WIPES 1
NDC: 78885-003 | Form: CLOTH
Manufacturer: ENSOBRETADOS Y DERIVADOS S.A. DE C.V.
Category: otc | Type: HUMAN OTC DRUG LABEL
Date: 20210301

ACTIVE INGREDIENTS: ALCOHOL 70 mL/100 mL
INACTIVE INGREDIENTS: GLYCERIN; WATER; ISOPROPYL ALCOHOL; FRAGRANCE LAVENDER ORC1800979

MKP SANITIZING ALCOHOL WIPES 1

ACTIVE INGREDIENT

Ethyl Alcohol 70%

PURPOSE

Antibacterial

USES

Hand sanitizer to decrease bacteria on the skin.

WARNINGS

For external use only. Flammable. Keep away from heat or flame.

Do not use

■ in children less than 2 months of age

■ on open skin wounds

When using this product keep out of eyes, ears, and mouth. In case of contact with eyes, rinse eyes thoroughly with water.

Stop use and ask a doctor if irritation or rash occurs. These may be signs of a serious condition.

Keep out of reach of children. If swallowed, get medical help or contact a Poison Control Center right away.

Keep out of reach of children If swallowed get medical help or contact a Poison Control Center right away.

DIRECTIONS

■ Wet hands thoroughly. Allow to dry without wiping.

■ Supervise children under 6 years of age when using this product to avoid swallowing.

OTHER INFORMATION

■ Store between 15-30C (59-86F)

■ Avoid freezing and excessive heat above 40C (104F)

INACTIVE INGREDIENTS

Water (Aqua), Isopropyl Alcohol, Glycerin, Fragrance.

QUESTIONS OR COMMENTS?

1-855-349-7735 or visit www.texasmedicaltechnology.com